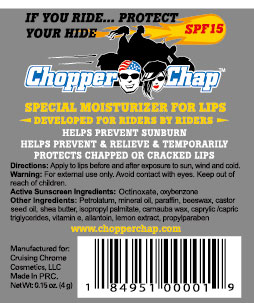 DRUG LABEL: Chopper Chap Lip Balm
NDC: 76464-001 | Form: STICK
Manufacturer: Cruising Chrome Cosmetics, LLC
Category: otc | Type: HUMAN OTC DRUG LABEL
Date: 20111128

ACTIVE INGREDIENTS: Octinoxate 70 mg/1 g; Oxybenzone 30 mg/1 g
INACTIVE INGREDIENTS: Petrolatum 450 mg/1 g; Mineral Oil 134 mg/1 g; Paraffin 100 mg/1 g; Yellow Wax 40 mg/1 g; Castor Oil 50 mg/1 g; Shea Butter 40 mg/1 g; ISOPROPYL PALMITATE 20 mg/1 g; Carnauba Wax 20 mg/1 g; MEDIUM-CHAIN TRIGLYCERIDES 20 mg/1 g; Alpha-Tocopherol 10 mg/1 g; ALLANTOIN 10 mg/1 g; PROPYLPARABEN 2 mg/1 g; LEMON 4 mg/1 g

Chopper Chap OTC Listing

Active Sunscreen Ingredients

Octinoxate, oxybenzone

Warning

For external use only. Avoid contact with eyes. Keep out of reach of children.

Other Ingredients

Petrolatum, mineral oil, paraffin, beeswax, castor seed oil, shea butter, isopropyl palmitate, carnauba wax, caprylic/capric triglycerides, vitamin e, allantoin, lemon extract, propylparaben